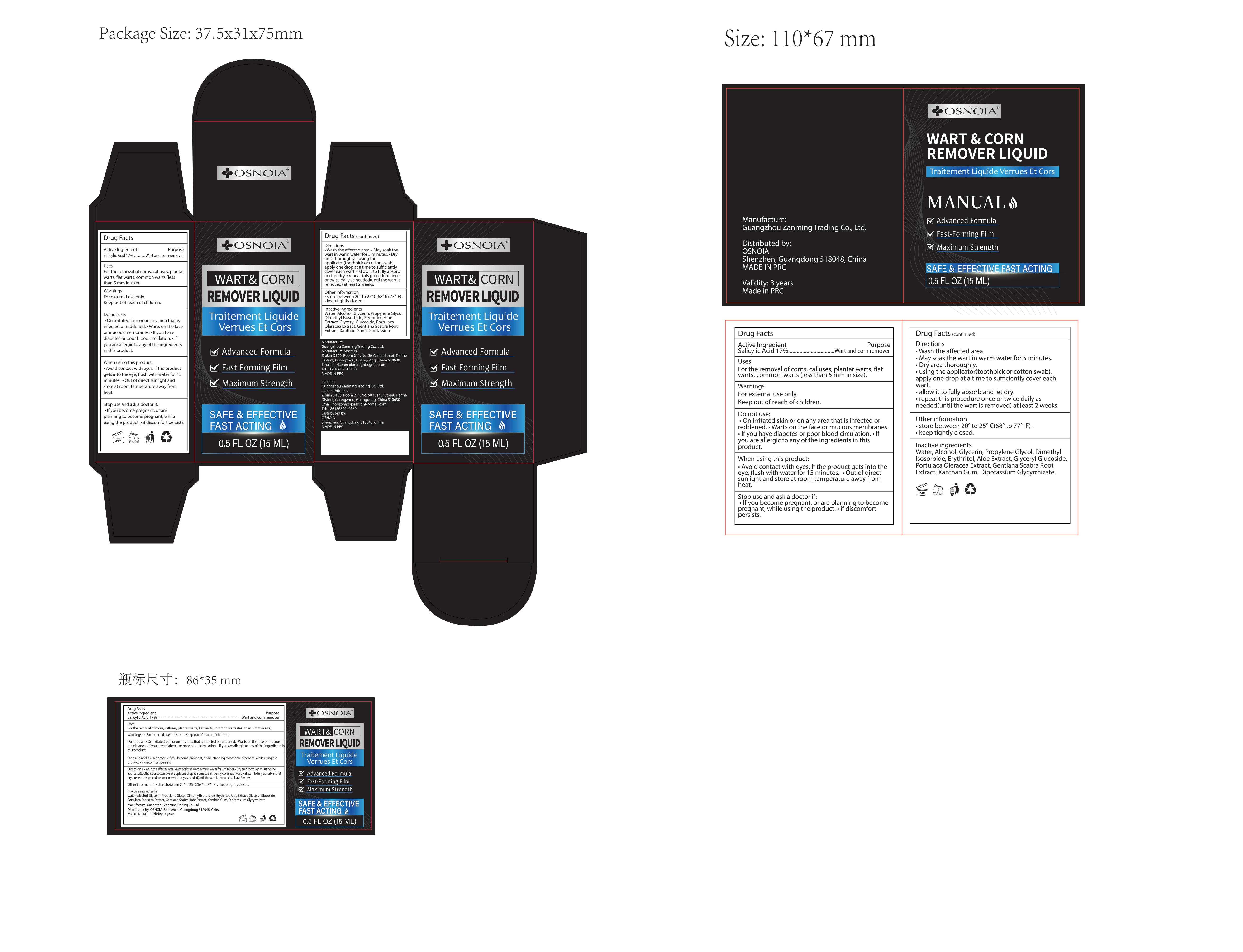 DRUG LABEL: OSNOIA Wart Remover
NDC: 85150-006 | Form: LIQUID
Manufacturer: Guangzhou Zanming Trading Co., Ltd.
Category: otc | Type: HUMAN OTC DRUG LABEL
Date: 20250422

ACTIVE INGREDIENTS: SALICYLIC ACID 17 g/100 mL
INACTIVE INGREDIENTS: XANTHAN GUM; DIMETHYL ISOSORBIDE; GLYCERIN; ERYTHRITOL; ALOE; GLYCERYL GLUCOSIDE; GLYCYRRHIZINATE DIPOTASSIUM; PROPYLENE GLYCOL; GENTIANA SCABRA ROOT; ALCOHOL; PURSLANE; WATER

85150-006

Active Ingredient

SALICYLIC ACID 17% W/W

Purpose

Wart and corn remover

Use

For the removal of corns, calluses, plantar warts, flat warts, common warts (less than 5 mm in size).

Warnings

For external use only.
Keep out of reach of children.

Do not use

• On irritated skin or on any area that is infected or reddened.

• Warts on the face or mucous membranes.

• If you have diabetes or poor blood circulation.

• If you are allergic to any of the ingredients in this product.

When Using

• Avoid contact with eyes. If the product gets into the eye, flush with water for 15 minutes.

• Out of direct sunlight and store at room temperature away from heat.

Stop Use

• If you become pregnant, or are planning to become pregnant, while using the product.

• if discomfort persists.

Ask Doctor

• If you become pregnant, or are planning to become pregnant, while using the product.

• if discomfort persists.

Keep Oot Of Reach Of Children

Keep out of reach of children.

Directions

• Wash the affected area.

• May soak the wart in warm water for 5 minutes.

• Dry area thoroughly.

• using the applicator(toothpick or cotton swab), apply one drop at a time to sufficiently cover each wart.

• allow it to fully absorb and let dry.

• repeat this procedure once or twice daily as needed(until the wart is removed) at least 2 weeks.

Other information

• store between 20° to 25° C(68° to 77° F) .

• keep tightly closed.

Inactive ingredients

Water, Alcohol, Glycerin, Propylene Glycol, Dimethyl Isosorbide, Erythritol, Aloe Extract, Glyceryl Glucoside, Portulaca Oleracea Extract, Gentiana Scabra Root Extract, Xanthan Gum, Dipotassium Glycyrrhizate.